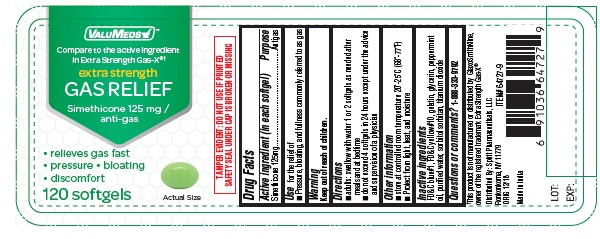 DRUG LABEL: Simethicone
NDC: 68210-3130 | Form: CAPSULE, LIQUID FILLED
Manufacturer: SPIRIT PHARMACEUTICALS LLC
Category: otc | Type: HUMAN OTC DRUG LABEL
Date: 20241211

ACTIVE INGREDIENTS: DIMETHICONE 125 mg/1 1
INACTIVE INGREDIENTS: D&C YELLOW NO. 10; FD&C BLUE NO. 1; GELATIN; GLYCERIN; PEPPERMINT OIL; SORBITAN; SORBITOL; TITANIUM DIOXIDE; WATER

Extra Strength Gas Relief

Active ingredient (in each softgel)

Simethicone 125mg

Purpose

Antigas

Use

for the relief of

- pressure, bloating, and fullness commonly referred to as gas

Directions

- adults: swallow with water 1 or 2 softgels as needed after meals and at bedtime
- do not exceed 4 softgels in 24 hours except under the advice and supervision of a physician

Other information

- store at controlled room temperature 20-25ºC (68-77ºF)
- protect from light, heat, and moisture

Inactive ingredients

FD&C blue 1, FD&C yello#10, gelatin, glycerin, peppermint oil, purified water, sorbitol sorbitan, titanium dioxide

Questions or comments?

1-888-333-9792

PRINCIPAL DISPLAY PANEL

Compare to the active ingredient
in Extra Strength Gas-X®†

Extra Strength Gas Relief

SIMETHICONE 125 MG / ANTIGAS

RELIEVES GAS FAST

PRESSURE

BLOATING

DISCOMFORT

†This product is not manufactured or distributed by GlaxoSmithKline,
owner of the registered trademark Extra Strength Gas-X®